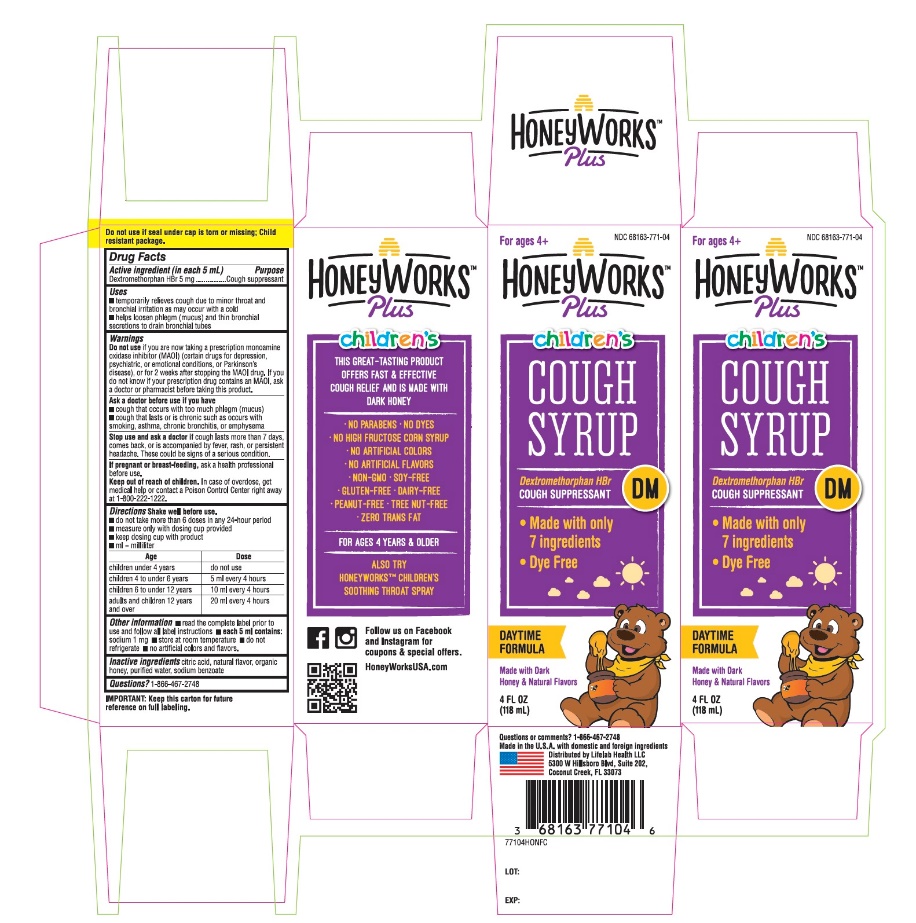 DRUG LABEL: Honey Works

NDC: 68163-771 | Form: SYRUP
Manufacturer: RARITAN PHARMACEUTICALS INC
Category: otc | Type: HUMAN OTC DRUG LABEL
Date: 20251014

ACTIVE INGREDIENTS: DEXTROMETHORPHAN HYDROBROMIDE 5 mg/5 mL
INACTIVE INGREDIENTS: ANHYDROUS CITRIC ACID; HONEY; WATER

Kids Honey Works™ Honey Cough Syrup

INDICATIONS AND USAGE

Active Ingredient (in each 5 mL)

Dextromethorphan HBr, USP 5 mg

Purpose

- Cough suppressant

Uses

- temporarily relieves cough due to minor throat and bronchial irritation as may occur with a cold
- helps loosen phlegm (mucus) and thin bronchial secretions to drain bronchial tubes

Warnings

DO NOT USE

Do not useif you are now taking a prescription monoamine oxidase inhibitor (MAOI) (certain drugs for depression, psychiatric, or emotional conditions, or Parkinson's disease), or for 2 weeks after stopping the MAOI drug. If you do not know if your prescription drug contains an MAOI, ask a doctor or pharmacist before taking this product.

Ask a doctor before use if you have

- cough that occurs with too much phlegm (mucus)
- cough that lasts or is chronic such as occurs with smoking, asthma, chronic bronchitis, or emphysema

Stop use and ask a doctor ifcough lasts more than 7 days, comes back, or is accompanied by fever, rash, or persistent headache. These could be signs of a serious condition.

PREGNANCY OR BREAST FEEDING

If pregnant or breast-feeding,ask a health professional before use.

Keep out of reach of children.In case of overdose, get medical help or contact a Poison Control Center right away at 1-800-222-1222.

Directions

- shake well before use
- do not take more than 6 doses in any 24-hour period
- measure only with dosing cup provided
- do not use dosing cup with other products
- ml = milliliter
- doses as follows or as directed by doctor

age | dose
children under 6 years | do not use
children 6 years to under 12 years | 5-10 mL every 4 hours

Other information

- store at room temperature. Do not refrigerate
- alcohol free

Inactive ingredients

Natural citric acid, natural flavor, organic honey, purified water

Questions or comments?

1-866-467-2748

PRINCIPAL DISPLAY PANEL - 118 ml Bottle Label

NDC# 68163-771-04

Kids Honey Works™

HONEY

Cough Syrup

Plus Dextromethorphan HBr

Cough Suppressant

- 100% U.S. Sourced Natural Honey
- For Ages 6 years +

Up to 6 Hours Relief

Clinically Proven Ingredient

Great Tasting Syrup

4 FL OZ (118 ml)

This great-tasting product offers fast & effective cough relief and is made with 100% U.S. sourced natural, dark honey.

Also try HoneyWorks™ Kids Soothing Throat Spray

- No Artificial Colors
- GMO-Free
- No Artificial Flavors
- Gluten-Free
- Soy-Free
- Dairy-Free
- Peanut-Free
- Tree Nut-Free
- Zero Trans Fat

Follow us on Facebook and Twitter for coupons & special offers.

Made in USA with domestic and foreign components

Distributed by: Lifelab Health LLC

6574 N. State Road 7 #361

Coconut Creek, FL 33073

IMPORTANT: Keep this carton for future reference on full labeling.